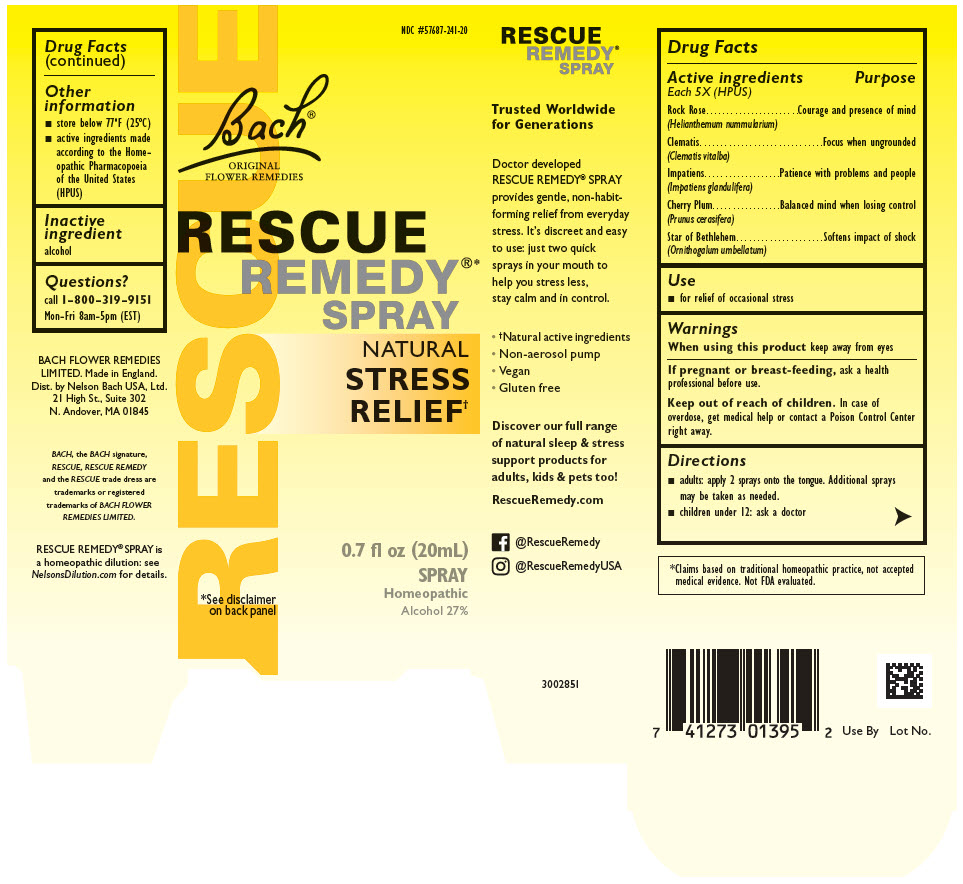 DRUG LABEL: Rescue Remedy
NDC: 57687-241 | Form: SOLUTION
Manufacturer: Nelson Bach USA, Ltd.
Category: homeopathic | Type: HUMAN OTC DRUG LABEL
Date: 20201019

ACTIVE INGREDIENTS: HELIANTHEMUM NUMMULARIUM WHOLE 5 [hp_X]/0.095 mL; CLEMATIS VITALBA WHOLE 5 [hp_X]/0.095 mL; IMPATIENS GLANDULIFERA WHOLE 5 [hp_X]/0.095 mL; PRUNUS CERASIFERA WHOLE 5 [hp_X]/0.095 mL; ORNITHOGALUM UMBELLATUM WHOLE 5 [hp_X]/0.095 mL
INACTIVE INGREDIENTS: ALCOHOL

RESCUE®
REMEDY

Drug Facts

ACTIVE INGREDIENT

Active ingredients Each 5X (HPUS) | Purpose
Rock Rose (Helianthemum nummularium) | Courage and presence of mind
Clematis (Clematis vitalba) | Focus when ungrounded
Impatiens (Impatiens glandulifera) | Patience with problems and people
Cherry Plum (Prunus cerasifera) | Balanced mind when losing control
Star of Bethlehem (Ornithogalum umbellatum) | Softens impact of shock

Use

- for relief of occasional stress

Warnings

When using this product keep away from eyes

PREGNANCY OR BREAST FEEDING

If pregnant or breast-feeding, ask a health professional before use.

Keep out of reach of children. In case of overdose, get medical help or contact a Poison Control Center right away.

Directions

- adults: apply 2 sprays onto the tongue. Additional sprays may be taken as needed.
- children under 12: ask a doctor

Other information

- store below 77ºF (25ºC)
- active ingredients made according to the Homeopathic Pharmacopoeia of the United States (HPUS)

Inactive ingredient

alcohol

Questions?

call 1-800-319-9151

Mon-Fri 8am-5pm (EST)

Dist. by Nelson Bach USA, Ltd.
21 High St., Suite 302
N. Andover, MA 01845

PRINCIPAL DISPLAY PANEL - 20 mL Bottle Carton

NDC #57687-241-20

Bach®
ORIGINAL
FLOWER REMEDIES

RESCUE
REMEDY®*
SPRAY

NATURAL
STRESS
RELIEF†

0.7 fl oz (20mL)
SPRAY
Homeopathic
Alcohol 27%

*See disclaimer
on back panel